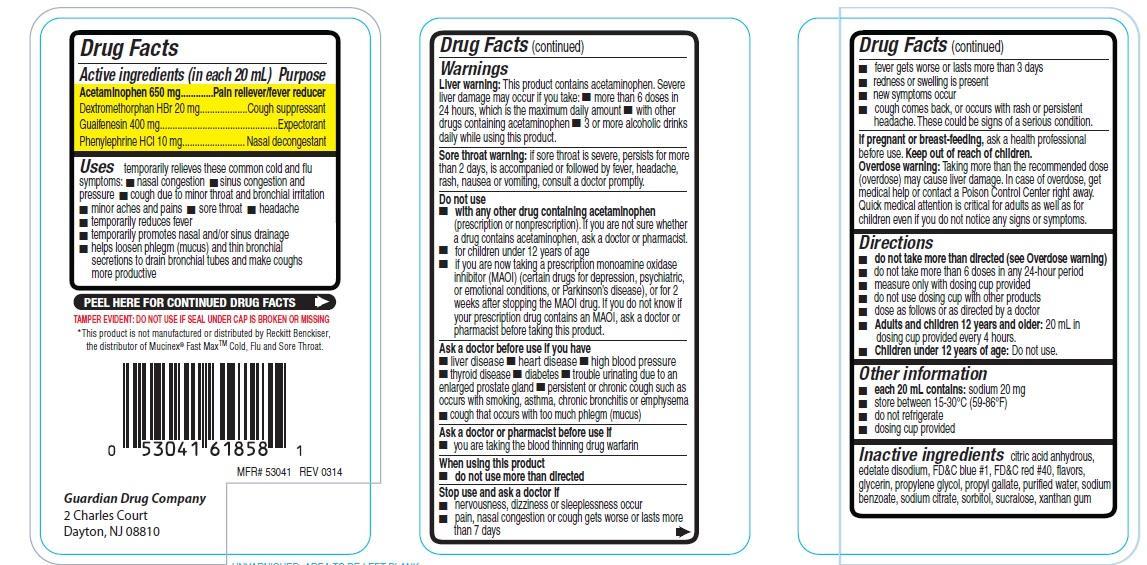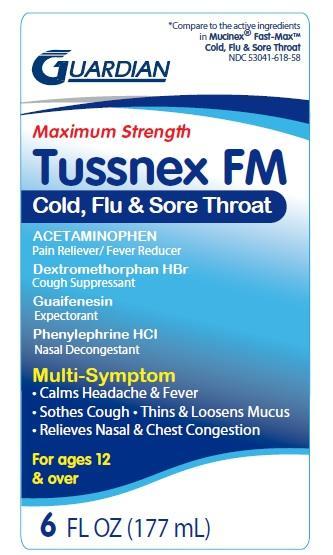 DRUG LABEL: Tussnex FM Cold, Flu and Sore Throat
NDC: 53041-618 | Form: LIQUID
Manufacturer: Guardian Drug Company
Category: otc | Type: HUMAN OTC DRUG LABEL
Date: 20241219

ACTIVE INGREDIENTS: ACETAMINOPHEN 650 mg/20 mL; DEXTROMETHORPHAN HYDROBROMIDE 20 mg/20 mL; GUAIFENESIN 400 mg/20 mL; PHENYLEPHRINE HYDROCHLORIDE 10 mg/20 mL
INACTIVE INGREDIENTS: ANHYDROUS CITRIC ACID; EDETATE DISODIUM; FD&C BLUE NO. 1; FD&C RED NO. 40; GLYCERIN; PROPYLENE GLYCOL; PROPYL GALLATE; WATER; SODIUM BENZOATE; SODIUM CITRATE; SORBITOL; SUCRALOSE; XANTHAN GUM

Maximum Strength Tussnex FM cold, flu and sore throat

Active ingredients (in each 20 mL)

Acetaminophen 650 mg

Dextromethorphan HBr 20 mg

Guaifenesin 400 mg

Phenylephrine HCl 10 mg

Purpose

Pain reliever/fever reducer

Cough suppressant

Expectorant

Nasal decongestant

Uses

- temporarily relieves these common cold and flu symptoms:
- nasal congestion
- sinus congestion and pressure
- cough due to minor throat and minor bronchial irritation
- minor aches and pains
- sore throat
- headache
- temporarily reduces fever
- temporarily promotes nasal and/or sinus drainage
- helps loosen phlegm (mucus) and thin bronchial secretions to drain bronchial tubes and make coughs more productive

Warnings

- Liver warning: This product contains acetaminophen. severe liver damage may occur if you take:
- more than 6 doses in 24 hours, which is maximum daily amount
- with other drugs containing acetaminophen
- 3 or more alcoholic drinks daily while using this product
- Sore throat warning: if sore throat is severe, persists for more than 2 days, is accompanied or followed by fever, headache, rash, nausea, vomiting, consult a doctor promptly.

Do not use

- with any other drug containing acetaminophen (prescription or non prescription). If you are not sure whether a drug contains acetaminophen, ask a doctor or pharmacist.
- for children under 12 years of age
- if you are now taking a prescription monoamine oxidase inhibitor (MAOI) (certain drugs for depression, psychiatric, or emotional conditions or parkinson's disease), or for 2 weeks after stopping the MAOI drug. If you do not know if your prescription drug contains an MAOI, ask a doctor or pharmacist before taking this product.

Ask a doctor before use if you have

- liver disease
- heart disease
- high blood pressure
- thyroid disease
- diabetes
- trouble urinating due to an enlarged prostate gland
- persistent or chronic cough such as occurs with smoking, asthma, chronic bronchitis or emphysema
- cough that occurs with too much phlegm (mucus)

Ask a doctor or pharmacist before use if

- you are taking the blood thinning drug warfarin

When using this product

- do not use more than directed

Stop use and ask a doctor if

- nervousness, dizziness or sleeplessness occur
- pain, nasal congestion or cough gets worse or lasts more than 7 days
- fever gets worse or lasts more than 3 days
- redness or swelling is present
- new symptoms occur
- cough comes back, or occurs with rash or persistent headache. These could be signs of a serious condition.

If pregnant or breast-feeding,

ask a health professional before use. Keep out of reach of children.

Overdose warning: Taking more than the recommended dose (overdose) may cause liver damage. In case of overdose, get medical help or contact a poison control center right away. Quick medical attention is critical for adults as well as for children even if you do not notice any signs or symptoms.

Directions

- do not take more than directed (see overdose warning)
- do not take more than 6 doses in any 24 hour period
- measure only with dosing cup provided
- do not use dosing cup with other products
- dose as follows or as directed by a doctor
- Adults and children 12 years and older: 20 mL in dosing cup provided every 4 hours.
- Children under 12 years of age: Do not use

Other information

- each 20 mL contains: sodium 20 mg
- store between 15-30oC(59-86oF)
- do not refrigerate
- dosing cup provided

Inactive ingredients

citric acid anhydrous, edetate disodium, FD and C blue 1, FD and C red 40, flavors, glycerin, propylene glycol, propyl gallate, purified water, sodium benzoate, sodium citrate, sorbitol, sucralose, xanthan gum

PDP

Compare to the active ingredients in Mucinex Fast Max Cold, Flu and Sore throat

Maxiumum strength Tussnex FM

Cold, Flu and Sore throat

Acetaminophen

Pain reliever / Fever Reducer

Dextromethorphan HBr

Cough Suppressant

Guaifenesin

Expectorant

Phenylephrine HCl

Nasal Decongestant

Calms headache and fever

Soothes cough

Thins and loosens mucus

Relieves Nasal and chest congestion

For ages 12 and over